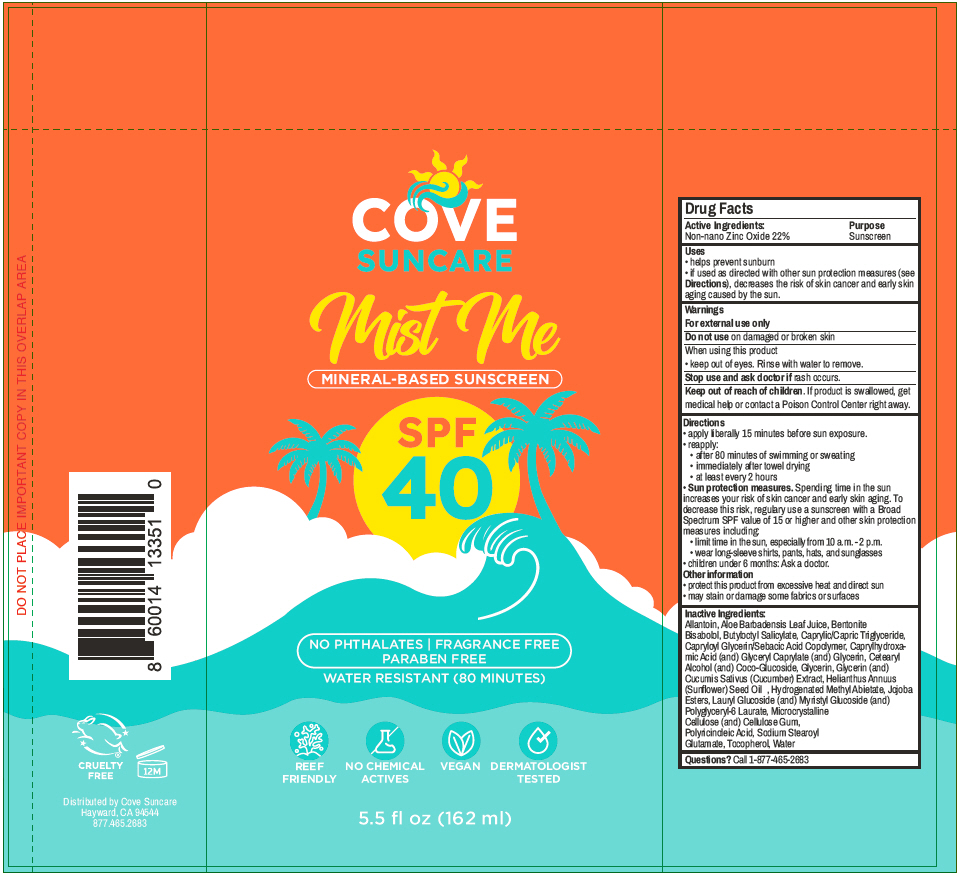 DRUG LABEL: Mist Me SPF-40
NDC: 85753-101 | Form: AEROSOL, SPRAY
Manufacturer: Cove Suncare LLC
Category: otc | Type: HUMAN OTC DRUG LABEL
Date: 20251009

ACTIVE INGREDIENTS: Zinc Oxide 22 g/100 mL
INACTIVE INGREDIENTS: WATER; Aloe Vera Leaf; Butyloctyl Salicylate; Sunflower Oil; Medium-Chain Triglycerides; Bentonite; Glycerin; Cetostearyl Alcohol; Coco-Glucoside; Hydrogenated Methyl Abietate; Capryloyl Glycerin/Sebacic Acid Copolymer (2000 Mpa.S); Microcrystalline Cellulose; Carboxymethylcellulose Sodium, Unspecified; Caprylhydroxamic Acid; Glyceryl Monocaprylate; Lauryl Glucoside; Myristyl Glucoside; Polyglyceryl-6 Laurate; Tocopherol; Levomenol; Allantoin; Sodium Stearoyl Glutamate

Mist Me SPF-40

Drug Facts

Active Ingredients

Non-nano Zinc Oxide 22%

Purpose

Sunscreen

Uses

- helps prevent sunburn
- if used as directed with other sun protection measures (see Directions), decreases the risk of skin cancer and early skin aging caused by the sun.

Warnings

For external use only

Do not use on damaged or broken skin

When using this product

- keep out of eyes. Rinse with water to remove.

Stop use and ask doctor if rash occurs.

Keep out of reach of children. If product is swallowed, get medical help or contact a Poison Control Center right away.

Directions

- apply liberally 15 minutes before sun exposure.
- reapply:
  - after 80 minutes of swimming or sweating
  - immediately after towel drying
  - at least every 2 hours
- Sun protection measures. Spending time in the sun increases your risk of skin cancer and early skin aging. To decrease this risk, regulary use a sunscreen with a Broad Spectrum SPF value of 15 or higher and other skin protection measures including:
  - limit time in the sun, especially from 10 a.m. - 2 p.m.
  - wear long-sleeve shirts, pants, hats, and sunglasses
- children under 6 months: Ask a doctor.

Other information

- protect this product from excessive heat and direct sun
- may stain or damage some fabrics or surfaces

Inactive Ingredients

Allantoin, Aloe Barbadensis Leaf Juice, Bentonite Bisabolol, Butyloctyl Salicylate, Caprylic/Capric Triglyceride, Capryloyl Glycerin/Sebacic Acid Copolymer, Caprylhydroxamic Acid (and) Glyceryl Caprylate (and) Glycerin, Cetearyl Alcohol (and) Coco-Glucoside, Glycerin, Glycerin (and) Cucumis Sativus (Cucumber) Extract, Helianthus Annuus (Sunflower) Seed Oil , Hydrogenated Methyl Abietate, Jojoba Esters, Lauryl Glucoside (and) Myristyl Glucoside (and) Polyglyceryl-6 Laurate, Microcrystalline Cellulose (and) Cellulose Gum, Polyricinoleic Acid, Sodium Stearoyl Glutamate, Tocopherol, Water

Questions?

Call 1-877-465-2683

Distributed by Cove Suncare
Hayward, CA 94544

PRINCIPAL DISPLAY PANEL - 162 ml Can Label

COVE
SUNCARE

Mist Me

MINERAL-BASED SUNSCREEN

SPF
40

NO PHTHALATES | FRAGRANCE FREE
PARABEN FREE

WATER RESISTANT (80 MINUTES)

REEF
FRIENDLY

NO CHEMICAL
ACTIVES

VEGAN

DERMATOLOGIST
TESTED

5.5 fl oz (162 ml)